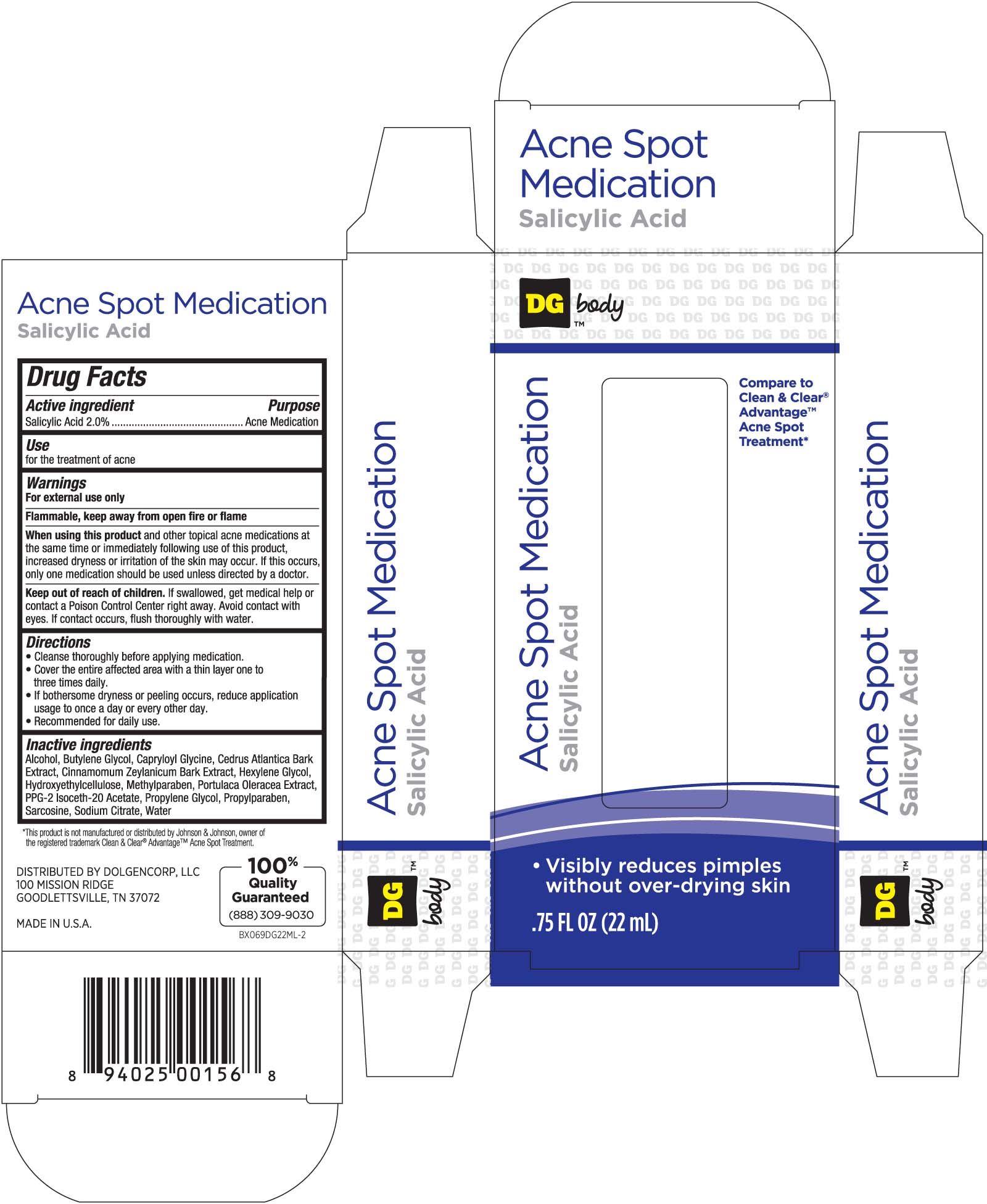 DRUG LABEL: Dollar General Acne Spot Medication
NDC: 55910-601 | Form: GEL
Manufacturer: DOLGENCORP, LLC 
Category: otc | Type: HUMAN OTC DRUG LABEL
Date: 20100710

ACTIVE INGREDIENTS: SALICYLIC ACID 20 mg/1 mL
INACTIVE INGREDIENTS: WATER; BUTYLENE GLYCOL; MANGANESE GLUCONATE; OLIVE OIL; CEDRUS ATLANTICA BARK; GLYCERIN; HEXYLENE GLYCOL; PURSLANE; ANHYDROUS TRISODIUM CITRATE; ALCOHOL; METHYLPARABEN; PROPYLPARABEN; HYDROXYETHYL CELLULOSE (4000 MPA.S FOR 1% AQUEOUS SOLUTION)

DRUG FACTS

Active ingredient Purpose
Salicylic Acid 2%............................................Acne medication

PURPOSE

Uses for the treatment of acne

Keep out of reach of children. If swallowed, get medical help or contact a
Poison Control Center right away. Avoid contact with eyes. If contact occurs,
flush thoroughly with water.

INDICATIONS AND USAGE

Uses for the treatment of acne

Warnings
For external use only
Flammable, keep away from open fire or flame
When using this product and other topical acne medications at the same time
or immediately following use of this product, increased dryness or irritation of the skin
may occur. If this occurs, only one medication should be used unless directed by a doctor.
Keep out of reach of children. If swallowed, get medical help or contact a Poison
Control Center right away. Avoid contact with eyes. If contact occurs, flush thoroughly with water.

Directions
- Cleanse skin thoroughly before applying medication
- Cover the affected area entirely up to three times daily
- If excessive dryness or peeling occurs, reduce usage to once a day or every other day
- Recommended for daily use

Inactive Ingredients
Alcohol, Butylene Glycol, Capryloyl Glycine, Cedrus Atlantic Bark Extract, Cinnamomum
Zeylanicum Bark Extract, Hexylene Glycol, Hydroxyethylcellulose, Methylparaben,
Portulica Oleracea Extract, PPG-2 Isoceth-20 Acetate, Propylene Glycol, Propylparaben,
Sarcosine, Sodium Citrate, Water